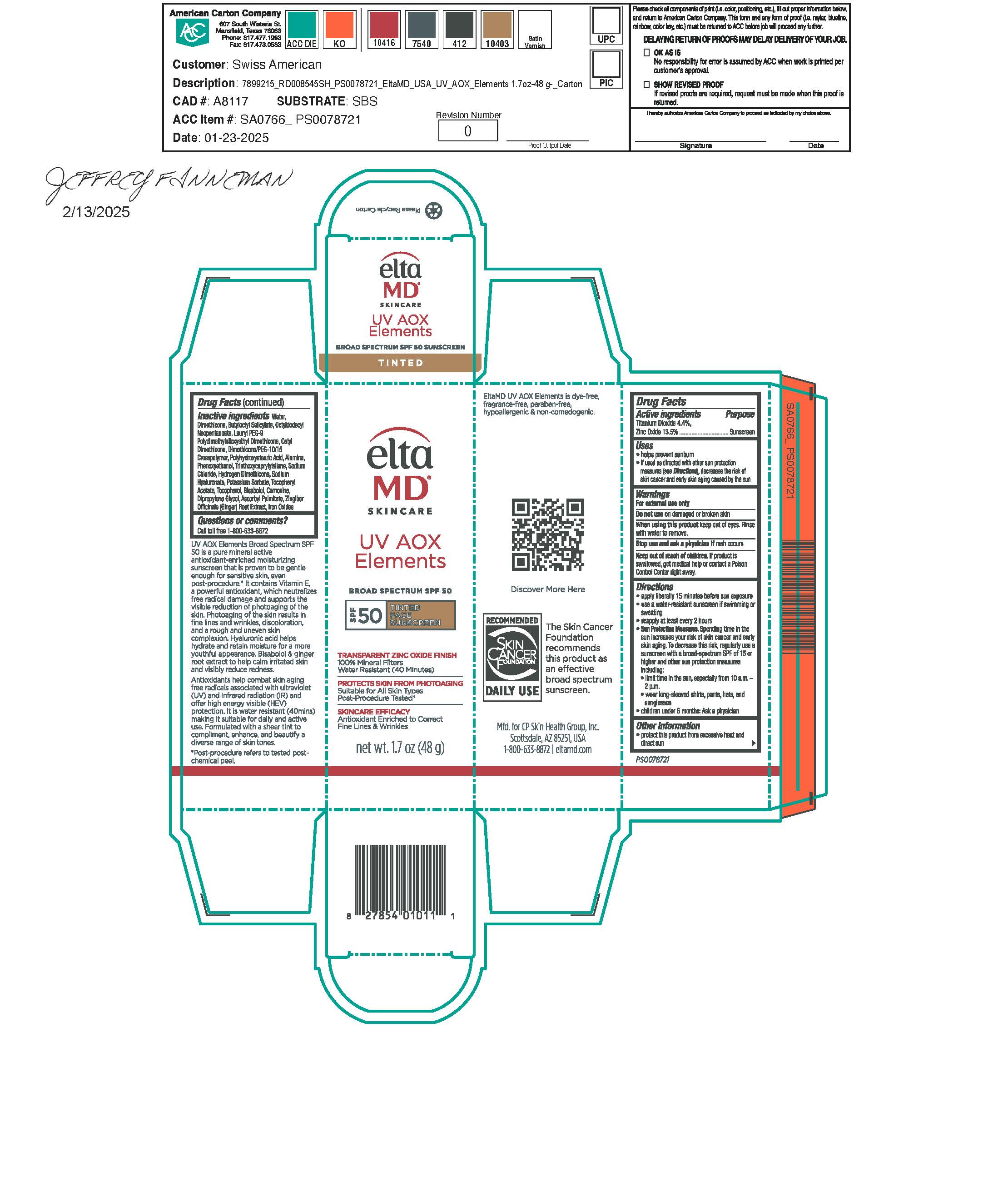 DRUG LABEL: EltaMD UV AOX Elements
NDC: 72043-2522 | Form: LOTION
Manufacturer: CP Skin Health Group, Inc
Category: otc | Type: HUMAN OTC DRUG LABEL
Date: 20250501

ACTIVE INGREDIENTS: ZINC OXIDE 135.1 g/1000 g; TITANIUM DIOXIDE 44.3 g/1000 g
INACTIVE INGREDIENTS: TRIETHOXYCAPRYLYLSILANE; WATER; POTASSIUM SORBATE; CARNOSINE; PHENOXYETHANOL; SODIUM CHLORIDE; CITRIC ACID; SODIUM HYALURONATE; DIMETHICONE; CETYL DIMETHICONE 45; ASCORBYL PALMITATE; DIMETHICONE/PEG-10/15 CROSSPOLYMER; LAURYL PEG-9 POLYDIMETHYLSILOXYETHYL DIMETHICONE; POLYHYDROXYSTEARIC ACID (2300 MW); OCTYLDODECYL NEOPENTANOATE; BUTYLOCTYL SALICYLATE; BISABOLOL; ZINGIBER OFFICINALE (GINGER) ROOT OIL; TOCOPHEROL; CANOLA OIL; FERROSOFERRIC OXIDE; FERRIC OXIDE YELLOW; FERRIC OXIDE RED; .ALPHA.-TOCOPHEROL ACETATE, DL-; ALUMINA; HYDROGEN DIMETHICONE (45 CST); DIPROPYLENE GLYCOL

UV AOX Elements Tinted

Warnings

For external use only. Do not use on damaged or broken skin. When using this product keep out of eyes. Rinse with water to remove. Stop use and ask a physician if rash occurs. If product is swallowed get medical help or contact a Poison Control Center right away.

Purpose

Sunscreen

Uses

Helps prevent sunburn. If used as directed with other sun protection measure (See Directions), decreases the risk of skin cancer and early skin aging caused by the sun.

Directions

Apply liberally 15 minutes before sun exposure. Use a water-resistant sunscreen if swimming or sweating. Reapply at least every 2 hours. Sun Protection Measures: Spending time in the sun increases your risk of skin cancer and early skin aging. To decrease this risk, regularly use a sunscreen with a broad-spectrum SPF of 15 or higher and other sun protection measures including: limit time in the sun, especially from 10 am to 2 pm. Wear long-sleeve shirts, pants, hats, and sunglasses. Children under 6 months: ask a physician.

Active Ingredients

Titanium Dioxide 4.4% Sunscreen
Zinc Oxide 13.5% Sunscreen

Keep out of reach of children

Inactive Ingredients

water, dimethicone, butyloctyl salicylate, octyldodecyl neopentanoate, lauryl PEG-9 polydimethylsiloxyethyl dimethicone, cetyl dimethicone, dimethicone/PEG-10/15 crosspolymer, polyhydroxystearic acid, alumina, phenoxyethanol, triethoxycaprylylsilane, sodium chloride, hydrogen dimethicone, sodium hyaluronate, potassium sorbate, tocopheryl acetate, tocopherol, bisabolol, carnosine, dipropylene glycol, ascorbyl palmitate, zingiber officinate (ginger) root extract, iron oxides

Other Information

Protect this product from excessive heat and direct sun.

Questions or Comments?

Call toll free 1-800-633-8872